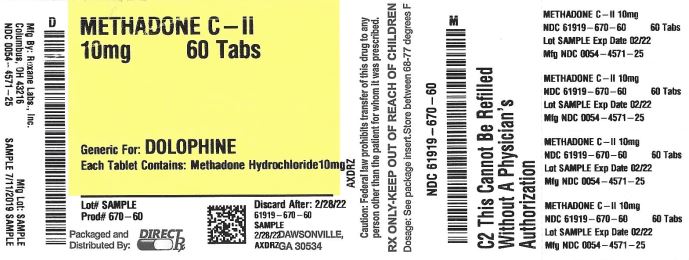 DRUG LABEL: METHADONE HYDROCHLORIDE
NDC: 61919-670 | Form: TABLET
Manufacturer: Direct_Rx
Category: prescription | Type: HUMAN PRESCRIPTION DRUG LABEL
Date: 20200120
DEA Schedule: CII

ACTIVE INGREDIENTS: METHADONE HYDROCHLORIDE 10 mg/1 1
INACTIVE INGREDIENTS: STARCH, CORN; MAGNESIUM STEARATE; CELLULOSE, MICROCRYSTALLINE

METHADONE HYDROCHLORIDE

BOXED WARNING

WARNING: ADDICTION, ABUSE AND MISUSE; LIFE-THREATENING RESPIRATORY DEPRESSION; ACCIDENTAL INGESTION; LIFE-THREATENING QT PROLONGATION; NEONATAL OPIOID WITHDRAWAL SYNDROME; and TREATMENT FOR OPIOID ADDICTION

Addiction, Abuse, and Misuse

Methadone hydrochloride tablets exposes patients and other users to the risks of opioid addiction, abuse, and misuse, which can lead to overdose and death. Assess each patient’s risk prior to prescribing methadone hydrochloride tablets, and monitor all patients regularly for the development of these behaviors or conditions [see Warnings and Precautions (5.1)].

Life-threatening Respiratory Depression

Serious, life-threatening, or fatal respiratory depression may occur with use of methadone hydrochloride tablets. Monitor for respiratory depression, especially during initiation of methadone hydrochloride tablets or following a dose increase [see Warnings and Precautions (5.2)].

Accidental Ingestion

Accidental ingestion of even one dose of methadone hydrochloride tablets, especially by children, can result in a fatal overdose of methadone [see Warnings and Precautions (5.2)].

Life-threatening QT Prolongation

QT interval prolongation and serious arrhythmia (torsades de pointes) have occurred during treatment with methadone. Most cases involve patients being treated for pain with large, multiple daily doses of methadone, although cases have been reported in patients receiving doses commonly used for maintenance treatment of opioid addiction. Closely monitor patients for changes in cardiac rhythm during initiation and titration of methadone hydrochloride tablets [see Warnings and Precautions (5.3)].

Neonatal Opioid Withdrawal Syndrome

Prolonged use of methadone hydrochloride tablets during pregnancy can result in neonatal opioid withdrawal syndrome, which may be life-threatening if not recognized and treated, and requires management according to protocols developed by neonatology experts. If opioid use is required for a prolonged period in a pregnant woman, advise the patient of the risk of neonatal opioid withdrawal syndrome and ensure that appropriate treatment will be available [see Warnings and Precautions (5.4)].

Conditions For Distribution And Use Of Methadone Products For The Treatment Of Opioid Addiction

For detoxification and maintenance of opioid dependence, methadone should be administered in accordance with the treatment standards cited in 42 CFR Section 8, including limitations on unsupervised administration [see Indications and Usage (1)].

INDICATIONS AND USAGE

Methadone hydrochloride tablets are indicated for the:

•
Management of pain severe enough to require daily, around-the-clock, long-term opioid treatment and for which alternative treatment options are inadequate.

Limitations of Use

•
Because of the risks of addiction, abuse, and misuse with opioids, even at recommended doses, and because of the greater risks of overdose and death with long-acting opioids, reserve methadone hydrochloride tablets for use in patients for whom alternative analgesic treatment options (e.g., non-opioid analgesics or immediate-release opioid analgesics) are ineffective, not tolerated, or would be otherwise inadequate to provide sufficient management of pain.
•
Methadone Hydrochloride Tablets USP are not indicated as an as-needed (prn) analgesic.
•
Detoxification treatment of opioid addiction (heroin or other morphine-like drugs).
•
Maintenance treatment of opioid addiction (heroin or other morphine-like drugs), in conjunction with appropriate social and medical services.

Conditions For Distribution And Use Of Methadone Products For The Treatment Of Opioid Addiction

Code of Federal Regulations, Title 42, Sec 8

Methadone products when used for the treatment of opioid addiction in detoxification or maintenance programs, shall be dispensed only by opioid treatment programs (and agencies, practitioners or institutions by formal agreement with the program sponsor) certified by the Substance Abuse and Mental Health Services Administration and approved by the designated state authority. Certified treatment programs shall dispense and use methadone in oral form only and according to the treatment requirements stipulated in the Federal Opioid Treatment Standards (42 CFR 8.12). See below for important regulatory exceptions to the general requirement for certification to provide opioid agonist treatment.

Failure to abide by the requirements in these regulations may result in criminal prosecution, seizure of the drug supply, revocation of the program approval, and injunction precluding operation of the program.

Regulatory Exceptions To The General Requirement For Certification To Provide Opioid Agonist Treatment: During inpatient care, when the patient was admitted for any condition other than concurrent opioid addiction (pursuant to 21CFR 1306.07(c)), to facilitate the treatment of the primary admitting diagnosis).

During an emergency period of no longer than 3 days while definitive care for the addiction is being sought in an appropriately licensed facility (pursuant to 21CFR 1306.07(b)).

DOSAGE AND ADMINISTRATION

2.1 Important General Information

•
The peak respiratory depressant effect of methadone occurs later and persists longer than its peak therapeutic effect.
•
A high degree of opioid tolerance does not eliminate the possibility of methadone overdose, iatrogenic or otherwise. Deaths have been reported during conversion to methadone from chronic, high-dose treatment with other opioid agonists and during initiation of methadone treatment of addiction in subjects previously abusing high doses of other agonists.
•
With repeated dosing, methadone is retained in the liver and then slowly released, prolonging the duration of potential toxicity.
•
Methadone has a narrow therapeutic index, especially when combined with other drugs.

2.2 Initial Dosing for Management of Pain

Methadone hydrochloride should be prescribed only by healthcare professionals who are knowledgeable in the use of potent opioids for the management of chronic pain.

Consider the following important factors that differentiate methadone from other opioid analgesics:

•
There is high interpatient variability in absorption, metabolism, and relative analgesic potency. Population-based equianalgesic conversion ratios between methadone and other opioids are not accurate when applied to individuals.
•
The duration of analgesic action of methadone is 4 to 8 hours (based on single-dose studies) but the plasma elimination half-life is 8 to 59 hours.
•
Steady-state plasma concentrations, and full analgesic effects, are not attained until at least 3 to 5 days on a dose, and may take longer in some patients.

Initiate the dosing regimen for each patient individually, taking into account the patient’s prior analgesic treatment experience and risk factors for addiction, abuse, and misuse [see Warnings and Precautions (5.1)]. Monitor patients closely for respiratory depression, especially within the first 24-72 hours of initiating therapy with methadone hydrochloride [see Warnings and Precautions (5.2)].

Use of Methadone Hydrochloride as the First Opioid Analgesic: Initiate treatment with methadone hydrochloride with 2.5 mg orally every 8 to 12 hours.

Conversion from Other Oral Opioids to Methadone Hydrochloride: Discontinue all other around-the-clock opioid drugs when methadone hydrochloride therapy is initiated. Deaths have occurred in opioid-tolerant patients during conversion to methadone.

While there are useful tables of opioid equivalents readily available, there is substantial inter-patient variability in the relative potency of different opioid drugs and products. As such, it is safer to underestimate a patient’s 24-hour oral methadone requirements and provide rescue medication (e.g., immediate-release opioid) than to overestimate the 24-hour oral methadone requirements which could result in adverse reactions. With repeated dosing, the potency of methadone increases due to systemic accumulation.

Consider the following when using the information in Table 1:

•
This is not a table of equinalgesic doses.
•
The conversion factors in this table are only for the conversion from another oral opioid analgesic to methadone hydrochloride.
•
The table cannot be used to convert from methadone hydrochloride to another opioid. Doing so will result in an overestimation of the dose of the new opioid and may result in fatal overdose.

Table 1: Conversion Factors to Methadone Hydrochloride

Total Daily Baseline Oral

Morphine Equivalent Dose

Estimated Daily Oral Methadone Requirement as Percent of Total Daily Morphine Equivalent Dose

< 100 mg

20% to 30%

100 to 300 mg

10% to 20%

300 to 600 mg

8% to 12%

600 mg to 1000 mg

5% to 10%

> 1000 mg

< 5 %

To calculate the estimated methadone hydrochloride dose using Table 1:

•
For patients on a single opioid, sum the current total daily dose of the opioid, convert it to a Morphine Equivalent Dose according to specific conversion factor for that specific opioid, then multiply the Morphine Equivalent Dose by the corresponding percentage in the above table to calculate the approximate oral methadone daily dose. Divide the total daily methadone dose derived from the table above to reflect the intended dosing schedule (i.e., for administration every 8 hours, divide total daily methadone dose by 3).
•
For patients on a regimen of more than one opioid, calculate the approximate oral methadone dose for each opioid and sum the totals to obtain the approximate total methadone daily dose. Divide the total daily methadone dose derived from the table above to reflect the intended dosing schedule (i.e., for administration every 8 hours, divide total daily methadone dose by 3).
•
For patients on a regimen of fixed-ratio opioid/non-opioid analgesic products, use only the opioid component of these products in the conversion.

Always round the dose down, if necessary, to the appropriate methadone hydrochloride strength(s) available.

Example conversion from a single opioid to methadone hydrochloride:

Step 1: Sum the total daily dose of the opioid (in this case, Morphine Extended Release Tablets 50 mg twice daily)
50 mg Morphine Extended Release Tablets 2 times daily = 100 mg total daily dose of Morphine
Step 2: Calculate the approximate equivalent dose of methadone hydrochloride based on the total daily dose of Morphine using Table 1.
100 mg total daily dose of Morphine x 15% (10% to 20% per Table 1) = 15 mg methadone hydrochloride daily
Step 3: Calculate the approximate starting dose of methadone hydrochloride to be given every 12 hours. Round down, if necessary, to the appropriate methadone hydrochloride tablets strengths available.
15 mg daily / 2 = 7.5 mg methadone hydrochloride every 12 hours
Then 7.5 mg is rounded down to 5 mg methadone hydrochloride every 12 hours

Close observation and frequent titration are warranted until pain management is stable on the new opioid. Monitor patients for signs and symptoms of opioid withdrawal or for signs of over-sedation/toxicity after converting patients to methadone hydrochloride.

Conversion from Parenteral Methadone to Methadone Hydrochloride: Use a conversion ratio of 1:2 mg for parenteral to oral methadone (e.g., 5 mg parenteral methadone to 10 mg oral methadone).

2.3 Titration and Maintenance of Therapy for Pain

Individually titrate methadone hydrochloride to a dose that provides adequate analgesia and minimizes adverse reactions. Continually reevaluate patients receiving methadone hydrochloride to assess the maintenance of pain control and the relative incidence of adverse reactions, as well as monitoring for the development of addiction, abuse, or misuse. Frequent communication is important among the prescriber, other members of the healthcare team, the patient, and the caregiver/family during periods of changing analgesic requirements, including initial titration. During chronic therapy, periodically reassess the continued need for the use of opioid analgesics.

Because of individual variability in the pharmacokinetic profile (i.e., terminal half-life (T1/2) from 8 to 59 hours in different studies [see Clinical Pharmacology (12.3)], titrate methadone slowly, with dose increases no more frequent than every 3 to 5 days. However, because of this high variability, some patients may require substantially longer periods between dose increases (up to 12 days). Monitor patients closely for the development of potentially life-threatening adverse reactions (e.g., CNS and respiratory depression).

Patients who experience breakthrough pain may require a dose increase of methadone hydrochloride, or may need rescue medication with an appropriate dose of an immediate-release medication. If the level of pain increases after dose stabilization, attempt to identify the source of increased pain before increasing the methadone hydrochloride dose.

If unacceptable opioid-related adverse reactions are observed, the subsequent doses may be reduced and/or the dosing interval adjusted (i.e., every 8 hours or every 12 hours). Adjust the dose to obtain an appropriate balance between management of pain and opioid-related adverse reactions.

2.4 Discontinuation of Methadone Hydrochloride for Pain

When a patient no longer requires therapy with methadone hydrochloride for pain, use a gradual downward titration, of the dose every two to four days, to prevent signs and symptoms of withdrawal in the physically-dependent patient. Do not abruptly discontinue methadone hydrochloride.

2.5 Induction/Initial Dosing for Detoxification and Maintenance Treatment of Opioid Addiction

For detoxification and maintenance of opioid dependence methadone should be administered in accordance with the

treatment standards cited in 42 CFR Section 8.12, including limitations on unsupervised administration.

Administer the initial methadone dose under supervision, when there are no signs of sedation or intoxication, and the patient shows symptoms of withdrawal. An initial single dose of 20 to 30 mg of methadone hydrochloride will often be sufficient to suppress withdrawal symptoms. The initial dose should not exceed 30 mg.

To make same-day dosing adjustments, have the patient wait 2 to 4 hours for further evaluation, when peak levels have been reached. Provide an additional 5 to 10 mg of methadone hydrochloride if withdrawal symptoms have not been suppressed or if symptoms reappear.

The total daily dose of methadone hydrochloride on the first day of treatment should not ordinarily exceed 40 mg. Adjust the dose over the first week of treatment based on control of withdrawal symptoms at the time of expected peak activity (e.g., 2 to 4 hours after dosing). When adjusting the dose, keep in mind that methadone levels will accumulate over the first several days of dosing; deaths have occurred in early treatment due to the cumulative effects. Instruct patients that the dose will “hold” for a longer period of time as tissue stores of methadone accumulate.

Use lower initial doses for patients whose tolerance is expected to be low at treatment entry. Any patient who has not taken opioids for more than 5 days may no longer be tolerant. Do not determine initial doses based on previous treatment episodes or dollars spent per day on illicit drug use.

Short-term Detoxification: For a brief course of stabilization followed by a period of medically supervised withdrawal, titrate the patient to a total daily dose of about 40 mg in divided doses to achieve an adequate stabilizing level. After 2 to 3 days of stabilization, gradually decrease the dose of methadone hydrochloride. Decrease the dose of methadone hydrochloride on a daily basis or at 2-day intervals, keeping the amount of methadone hydrochloride sufficient to keep withdrawal symptoms at a tolerable level. Hospitalized patients may tolerate a daily reduction of 20% of the total daily dose. Ambulatory patients may need a slower schedule.

2.6 Titration and Maintenance Treatment of Opioid Dependence Detoxification

Titrate patients in maintenance treatment to a dose that prevents opioid withdrawal symptoms for 24 hours, reduces drug hunger or craving, and blocks or attenuates the euphoric effects of self-administered opioids, ensuring that the patient is tolerant to the sedative effects of methadone. Most commonly, clinical stability is achieved at doses between 80 to 120 mg/day.

2.7Medically Supervised Withdrawal After a Period of Maintenance Treatment for Opioid Addiction

There is considerable variability in the appropriate rate of methadone taper in patients choosing medically supervised withdrawal from methadone treatment. Dose reductions should generally be less than 10% of the established tolerance or maintenance dose, and 10 to 14-day intervals should elapse between dose reductions. Apprise patients of the high risk of relapse to illicit drug use associated with discontinuation of methadone maintenance treatment.

2.8 Risk of Relapse in Patients on Methadone Maintenance Treatment of Opioid Addiction

Abrupt opioid discontinuation can lead to development of opioid withdrawal symptoms [see Drug Abuse and Dependence (9.3)]. Opioid withdrawal symptoms have been associated with an increased risk of relapse to illicit drug use in susceptible patients.

2.9 Considerations for Management of Acute Pain During Methadone Maintenance Treatment

Patients in methadone maintenance treatment for opioid dependence who experience physical trauma, postoperative pain or other acute pain cannot be expected to derive analgesia from their existing dose of methadone. Such patients should be administered analgesics, including opioids, in doses that would otherwise be indicated for non-methadone-treated patients with similar painful conditions. When opioids are required for management of acute pain in methadone maintenance patients, somewhat higher and/or more frequent doses will often be required than would be the case for non-tolerant patients due to the opioid tolerance induced by methadone.

2.10 Dosage Adjustment During Pregnancy

Methadone clearance may be increased during pregnancy. During pregnancy, a woman’s methadone dose may need to be increased or the dosing interval decreased. Methadone should be used in pregnancy only if the potential benefit justifies the potential risk to the fetus [see Use in Specific Populations (8.1)].

DOSAGE FORMS AND STRENGTHS

Methadone Hydrochloride Tablets USP are available in 5 mg and 10 mg dosage strengths. The 5 mg tablets are round, white, biconvex and are debossed with product identification “54” above “210” on one side and scored on the other side. The 10 mg tablets are round, white, biconvex and are debossed with product identification “54” above “142” on one side and scored on the other side.

CONTRAINDICATIONS

Methadone hydrochloride tablets are contraindicated in patients with:

•
Significant respiratory depression
•
Acute or severe bronchial asthma in an unmonitored setting or in the absence of resuscitative equipment
•
Known or suspected paralytic ileus

Hypersensitivity (e.g., anaphylaxis) to methadone [see Adverse Reactions (6)].

WARNINGS AND PRECAUTIONS

5.1 Addiction, Abuse and Misuse

Methadone hydrochloride tablets contain methadone, a Schedule II controlled substance. As an opioid, methadone hydrochloride exposes users to the risks of addiction, abuse, and misuse [see Drug Abuse and Dependence (9)]. As long-acting opioids such as methadone hydrochloride have pharmacological effects over an extended period of time, there is a greater risk for overdose and death.

Although the risk of addiction in any individual is unknown, it can occur in patients appropriately prescribed methadone hydrochloride and in those who obtain the drug illicitly. Addiction can occur at recommended doses and if the drug is misused or abused.

Assess each patient’s risk for opioid addiction, abuse, or misuse prior to prescribing methadone hydrochloride, and monitor all patients receiving methadone hydrochloride for the development of these behaviors or conditions. Risks are increased in patients with a personal or family history of substance abuse (including drug or alcohol addiction or abuse) or mental illness (e.g., major depression). The potential for these risks should not, however, prevent the prescribing of methadone hydrochloride for the proper management of pain in any given patient. Patients at increased risk may be prescribed long-acting opioids such as methadone hydrochloride, but use in such patients necessitates intensive counseling about the risks and proper use of methadone hydrochloride along with the intensive monitoring for signs of addiction, abuse, and misuse.

Abuse or misuse of methadone hydrochloride by crushing, chewing, snorting, or injecting the dissolved product will result in the uncontrolled delivery of the methadone and can result in overdose and death [see Overdosage (10)].

Opioid agonists such as methadone hydrochloride are sought by drug abusers and people with addiction disorders and are subject to criminal diversion. Consider these risks when prescribing or dispensing methadone hydrochloride. Strategies to reduce these risks include prescribing the drug in the smallest appropriate quantity and advising the patient on the proper disposal of unused drug [see Patient Counseling Information (17)]. Contact local state professional licensing board or state controlled substances authority for information on how to prevent and detect abuse or diversion of this product.

5.2 Life Threatening Respiratory Depression

Serious, life-threatening, or fatal respiratory depression has been reported with the use of long-acting opioids, even when used as recommended. Respiratory depression from opioid use, if not immediately recognized and treated, may lead to respiratory arrest and death. Management of respiratory depression may include close observation, supportive measures, and use of opioid antagonists, depending on the patient’s clinical status [see Overdosage (10)]. Carbon dioxide (CO2) retention from opioid-induced respiratory depression can exacerbate the sedating effects of opioids.

While serious, life-threatening, or fatal respiratory depression can occur at any time during the use of methadone hydrochloride, the risk is greatest during the initiation of therapy or following a dose increase. The peak respiratory depressant effect of methadone occurs later, and persists longer than the peak analgesic effect, especially during the initial dosing period. Closely monitor patients for respiratory depression when initiating therapy with methadone hydrochloride and following dose increases.

To reduce the risk of respiratory depression, proper dosing and titration of methadone hydrochloride are essential [see Dosage and Administration (2.2, 2.3)]. Overestimating the methadone hydrochloride dose when converting patients from another opioid product can result in fatal overdose with the first dose.

Accidental ingestion of even one dose of methadone hydrochloride, especially by children, can result in respiratory depression and death due to overdose of methadone.

5.3 Life-Threatening QT Prolongation

Cases of QT interval prolongation and serious arrhythmia (torsades de pointes) have been observed during treatment with methadone. These cases appear to be more commonly associated with, but not limited to, higher dose treatment (> 200 mg/day). Most cases involve patients being treated for pain with large, multiple daily doses of methadone, although cases have been reported in patients receiving doses commonly used for maintenance treatment of opioid addiction. In most patients on the lower doses typically used for maintenance, concomitant medications and/or clinical conditions such as hypokalemia were noted as contributing factors. However, the evidence strongly suggests that methadone possesses the potential for adverse cardiac conduction effects in some patients. The effects of methadone on the QT interval have been confirmed in in vivo laboratory studies, and methadone has been shown to inhibit cardiac potassium channels in in vitro studies.

Closely monitor patients with risk factors for development of prolonged QT interval (e.g., cardiac hypertrophy, concomitant diuretic use, hypokalemia, hypomagnesemia), a history of cardiac conduction abnormalities, and those taking medications affecting cardiac conduction. QT prolongation has also been reported in patients with no prior cardiac history who have received high doses of methadone.

Evaluate patients developing QT prolongation while on methadone treatment for the presence of modifiable risk factors, such as concomitant medications with cardiac effects, drugs that might cause electrolyte abnormalities, and drugs that might act as inhibitors of methadone metabolism.

Only initiate methadone hydrochloride therapy for pain in patients for whom the anticipated benefit outweighs the risk of QT prolongation and development of dysrhythmias that have been reported with high doses of methadone.

The use of methadone in patients already known to have a prolonged QT interval has not been systematically studied.

5.4 Neonatal Opioid Withdrawal Syndrome

Prolonged use of methadone hydrochloride during pregnancy can result in withdrawal signs in the neonate. Neonatal opioid withdrawal syndrome, unlike opioid withdrawal syndrome in adults, may be life-threatening if not recognized and treated, and requires management according to protocols developed by neonatology experts. If opioid use is required for a prolonged period in a pregnant woman, advise the patient of the risk of neonatal opioid withdrawal syndrome and ensure that appropriate treatment will be available.

Neonatal opioid withdrawal syndrome presents as irritability, hyperactivity and abnormal sleep pattern, high pitched cry, tremor, vomiting, diarrhea and failure to gain weight. The onset, duration, and severity of neonatal opioid withdrawal syndrome vary based on the specific opioid used, duration of use, timing and amount of last maternal use, and rate of elimination of the drug by the newborn [see Use in Special Populations (8.1)].

5.5 Interactions with Central Nervous System Depressants

Hypotension, profound sedation, coma, respiratory depression, and death may result if methadone hydrochloride is used concomitantly with alcohol or other central nervous system (CNS) depressants (e.g., sedatives, anxiolytics, hypnotics, neuroleptics, other opioids).

When considering the use of methadone hydrochloride in a patient taking a CNS depressant, assess the duration of use of the CNS depressant and the patient’s response, including the degree of tolerance that has developed to CNS depression. Additionally, evaluate the patient’s use of alcohol or illicit drugs that cause CNS depression. If the decision to begin methadone hydrochloride is made, start with methadone hydrochloride 2.5 mg every 12 hours, monitor patients for signs of sedation and respiratory depression, and consider using a lower dose of the concomitant CNS depressant [see Drug Interactions (7.1)].

5.6 Use in Elderly, Cachectic, and Debilitated Patients

Life-threatening respiratory depression is more likely to occur in elderly, cachectic, or debilitated patients as they may have altered pharmacokinetics or altered clearance compared to younger, healthier patients. Monitor such patients closely, particularly when initiating and titrating methadone hydrochloride and when methadone hydrochloride is given concomitantly with other drugs that depress respiration [see Warnings and Precautions (5.2)].

5.7 Use in Patients with Chronic Pulmonary Disease

Monitor patients with significant chronic obstructive pulmonary disease or cor pulmonale, and patients having a substantially decreased respiratory reserve, hypoxia, hypercapnia, or pre-existing respiratory depression for respiratory depression, particularly when initiating therapy and titrating with methadone hydrochloride, as in these patients, even usual therapeutic doses of methadone hydrochloride may decrease respiratory drive to the point of apnea [see Warnings and Precautions (5.2)]. Consider the use of alternative non-opioid analgesics in these patients if possible.

5.8 Hypotensive Effect

Methadone hydrochloride may cause severe hypotension including orthostatic hypotension and syncope in ambulatory patients. There is an increased risk in patients whose ability to maintain blood pressure has already been compromised by a reduced blood volume or concurrent administration of certain CNS depressant drugs (e.g. phenothiazines or general anesthetics) [see Drug Interactions (7.1)]. Monitor these patients for signs of hypotension after initiating or titrating the dose of methadone hydrochloride.

5.9 Use in Patients with Head Injury or Increased Intracranial Pressure

Monitor patients taking methadone hydrochloride who may be susceptible to the intracranial effects of CO2 retention (e.g., those with evidence of increased intracranial pressure or brain tumors) for signs of sedation and respiratory depression, particularly when initiating therapy with methadone hydrochloride. Methadone hydrochloride may reduce respiratory drive, and the resultant CO2 retention can further increase intracranial pressure. Opioids may also obscure the clinical course in a patient with a head injury.

Avoid the use of methadone hydrochloride in patients with impaired consciousness or coma.

5.10 Use in Patients with Gastrointestinal Conditions

Methadone hydrochloride is contraindicated in patients with paralytic ileus. Avoid the use of methadone hydrochloride in patients with other gastrointestinal obstruction.

The methadone in methadone hydrochloride may cause spasm of the sphincter of Oddi. Monitor patients with biliary tract disease, including acute pancreatitis, for worsening symptoms. Opioids may cause increases in the serum amylase.

5.11 Use in Patients with Convulsive or Seizure Disorders

The methadone in methadone hydrochloride may aggravate convulsions in patients with convulsive disorders, and may induce or aggravate seizures in some clinical settings. Monitor patients with a history of seizure disorders for worsened seizure control during methadone hydrochloride therapy.

5.12 Avoidance of Withdrawal

Avoid the use of partial agonists or mixed agonist/antagonist (i.e., buprenorphine, pentazocine, nalbuphine and butorphanol) in patients who have received or are receiving a course of therapy with a full opioid agonist analgesic, including methadone hydrochloride. In these patients, mixed agonists/antagonist and partial agonist analgesics may reduce the analgesic effect and/or may precipitate withdrawal symptoms [see Drug Interactions (7.4)].

When discontinuing methadone hydrochloride, gradually taper the dose [see Dosage and Administration (2.4)]. Do not abruptly discontinue methadone hydrochloride.

5.13 Driving and Operating Machinery

Methadone hydrochloride may impair the mental or physical abilities needed to perform potentially hazardous activities such as driving a car or operating machinery. Warn patients not to drive or operate dangerous machinery unless they are tolerant to the effects of methadone hydrochloride and know how they will react to the medication.

ADVERSE REACTIONS

The following serious adverse reactions are discussed elsewhere in the labeling:

•
Addiction, Abuse, and Misuse [see Warnings and Precautions (5.1)]
•
Life Threatening Respiratory Depression [see Warnings and Precautions (5.2)]
•
QT Prolongation [see Warnings and Precautions (5.3)]
•
Neonatal Opioid Withdrawal Syndrome [see Warnings and Precautions (5.4)]
•
Interactions with Other CNS Depressants [see Warnings and Precautions (5.5)]
•
Hypotensive Effect [see Warnings and Precautions (5.8)]
•
Gastrointestinal Effects [see Warnings and Precautions (5.10)]
•
Seizures [see Warnings and Precautions (5.11)]

The major hazards of methadone are respiratory depression and, to a lesser degree, systemic hypotension. Respiratory arrest, shock, cardiac arrest, and death have occurred.

The most frequently observed adverse reactions include lightheadedness, dizziness, sedation, nausea, vomiting, and sweating. These effects seem to be more prominent in ambulatory patients and in those who are not suffering severe pain. In such individuals, lower doses are advisable.

Other adverse reactions include the following:

Body as a Whole: asthenia (weakness), edema, headache

Cardiovascular: arrhythmias, bigeminal rhythms, bradycardia, cardiomyopathy, ECG abnormalities, extrasystoles, flushing, heart failure, hypotension, palpitations, phlebitis, QT interval prolongation, syncope, T-wave inversion, tachycardia, torsades de pointes, ventricular fibrillation, ventricular tachycardia

Central Nervous System: agitation, confusion, disorientation, dysphoria, euphoria, insomnia, hallucinations, seizures, visual disturbances

Endocrine: hypogonadism

Gastrointestinal: abdominal pain, anorexia, biliary tract spasm, constipation, dry mouth, glossitis

Hematologic: reversible thrombocytopenia has been described in opioid addicts with chronic hepatitis

Metabolic: hypokalemia, hypomagnesemia, weight gain

Renal: antidiuretic effect, urinary retention or hesitancy

Reproductive: amenorrhea, reduced libido and/or potency, reduced ejaculate volume, reduced seminal vesicle and prostate secretions, decreased sperm motility, abnormalities in sperm morphology

Respiratory: pulmonary edema, respiratory depression

Skin and Subcutaneous Tissue: pruritus, urticaria, other skin rashes, and rarely, hemorrhagic urticaria

Hypersensitivity: Anaphylaxis has been reported with ingredients contained in methadone hydrochloride. Advise patients how to recognize such a reaction and when to seek medical attention.

Maintenance on a Stabilized Dose: During prolonged administration of methadone, as in a methadone maintenance treatment program, constipation and sweating often persist and hypogonadism, decreased serum testosterone and reproductive effects are thought to be related to chronic opioid use.

Methadone Hydrochloride for the Detoxification and Maintenance Treatment of Opioid Dependence: During the induction phase of methadone maintenance treatment, patients are being withdrawn from illicit opioids and may have opioid withdrawal symptoms. Monitor patients for signs and symptoms including: lacrimation, rhinorrhea, sneezing, yawning, excessive perspiration, goose-flesh, fever, chilling alternating with flushing, restlessness, irritability, weakness, anxiety, depression, dilated pupils, tremors, tachycardia, abdominal cramps, body aches, involuntary twitching and kicking movements, anorexia, nausea, vomiting, diarrhea, intestinal spasms, and weight loss and consider dose adjustment as indicated.

DRUG INTERACTIONS

7.1 CNS Depressants

The concomitant use of methadone hydrochloride with other CNS depressants including sedatives, hypnotics, tranquilizers, general anesthetics, phenothiazines, other opioids, and alcohol can increase the risk of respiratory depression, profound sedation, coma and death. Monitor patients receiving CNS depressants and methadone hydrochloride for signs of respiratory depression, sedation and hypotension.

When combined therapy with any of the above medications is considered, the dose of one or both agents should be reduced [Warnings and Precautions (5.5)].

Deaths have been reported when methadone has been abused in conjunction with benzodiazepines.

7.2 Drugs Affecting Cytochrome P450 Isoenzymes

Methadone undergoes hepatic N-demethylation by cytochrome P450 (CYP) isoforms, principally CYP3A4, CYP2B6, CYP2C19, and to a lesser extent by CYP2C9 and CYP2D6 [see Clinical Pharmacology (12.3)].

Inhibitors of CYP3A4 and 2C9: Because the CYP3A4 isoenzyme plays a major role in the metabolism of methadone, drugs that inhibit CYP3A4 activity may cause decreased clearance of methadone which could lead to an increase in methadone plasma concentrations and result in increased or prolonged opioid effects. These effects could be more pronounced with concomitant use of CYP 2C9 and 3A4 inhibitors. If co-administration with methadone hydrochloride is necessary, monitor patients for respiratory depression and sedation at frequent intervals and consider dose adjustments until stable drug effects are achieved [see Clinical Pharmacology (12.3)].

Inducers of CYP3A4: CYP450 3A4 inducers may induce the metabolism of methadone and, therefore, may cause increased clearance of the drug which could lead to a decrease in methadone plasma concentrations, lack of efficacy or, possibly, development of a withdrawal syndrome in a patient who had developed physical dependence to methadone. If co-administration with methadone hydrochloride is necessary, monitor for signs of opioid withdrawal and consider dose adjustments until stable drug effects are achieved [see Clinical Pharmacology (12.3)].

After stopping the treatment of a CYP3A4 inducer, as the effects of the inducer decline, methadone plasma concentration will increase which could increase or prolong both the therapeutic and adverse effects, and may cause serious respiratory depression. If co-administration or discontinuation of a CYP3A4 inducer with methadone hydrochloride is necessary, monitor for signs of opioid withdrawal and consider dose adjustments until stable drug effects are achieved [see Clinical Pharmacology (12.3)].

Paradoxical Effects of Antiretroviral Agents on Methadone Hydrochloride: Concurrent use of certain antiretroviral agents with CYP3A4 inhibitory activity, alone and in combination, such as abacavir, amprenavir, darunavir+ritonavir, efavirenz, nelfinavir, nevirapine, ritonavir, telaprevir, lopinavir+ritonavir, saquinavir+ritonavir, and tipranvir+ritonavir, has resulted in increased clearance or decreased plasma levels of methadone. This may result in reduced efficacy of methadone hydrochloride and could precipitate a withdrawal syndrome. Monitor methadone-maintained patients receiving any of these anti-retroviral therapies closely for evidence of withdrawal effects and adjust the methadone dose accordingly.

Effects of Methadone Hydrochloride on Antiretroviral Agents: Didanosine and Stavudine: Experimental evidence demonstrated that methadone decreased the area under the concentration-time curve (AUC) and peak levels for didanosine and stavudine, with a more significant decrease for didanosine. Methadone disposition was not substantially altered.

Zidovudine: Experimental evidence demonstrated that methadone increased the AUC of zidovudine, which could result in toxic effects.

7.3 Potentially Arrhythmogenic Agents

Monitor patients closely for cardiac conduction changes when any drug known to have the potential to prolong the QT interval is prescribed in conjunction with methadone. Pharmacodynamic interactions may occur with concomitant use of methadone and potentially arrhythmogenic agents such as class I and III antiarrhythmics, some neuroleptics and tricyclic antidepressants, and calcium channel blockers.

Similarly, monitor patients closely when prescribing methadone concomitantly with drugs capable of inducing electrolyte disturbances (hypomagnesemia, hypokalemia) that may prolong the QT interval, including diuretics, laxatives, and, in rare cases, mineralocorticoid hormones.

7.4 Mixed Agonist/Antagonist and Partial Agonist Opioid Analgesics

Mixed agonist/antagonist (i.e., pentazocine, nalbuphine and butorphanol) and partial agonist (buprenorphine) analgesics may reduce the analgesic effect of methadone hydrochloride or precipitate withdrawal symptoms. Avoid the use of mixed agonist/antagonist and partial agonist analgesics in patients receiving methadone hydrochloride.

7.5 Antidepressants

Monoamine Oxidase (MAO) Inhibitors: Therapeutic doses of meperidine have precipitated severe reactions in patients concurrently receiving monoamine oxidase inhibitors or those who have received such agents within 14 days. Similar reactions thus far have not been reported with methadone. However, if the use of methadone is necessary in such patients, a sensitivity test should be performed in which repeated small, incremental doses of methadone are administered over the course of several hours while the patient’s condition and vital signs are carefully observed.

Desipramine: Blood levels of desipramine have increased with concurrent methadone administration.

7.6 Anticholinergics

Anticholinergics or other drugs with anticholinergic activity when used concurrently with opioids may result in increased risk of urinary retention and/or severe constipation, which may lead to paralytic ileus. Monitor patients for signs of urinary retention or reduced gastric motility when methadone hydrochloride is used concurrently with anticholinergic drugs.

7.7 Laboratory Test Interactions

False positive urine drug screens for methadone have been reported for several drugs including diphenhydramine, doxylamine, clomipramine, chlorpromazine, thioridazine, quetiapine, and verapamil.

USE IN SPECIFIC POPULATIONS

8.1 Pregnancy

Clinical Considerations: Fetal/neonatal adverse reactions: Prolonged use of opioid analgesics during pregnancy for medical or nonmedical purposes can result in physical dependence in the neonate and neonatal opioid withdrawal syndrome shortly after birth. Observe newborns for symptoms of neonatal opioid withdrawal syndrome, such as poor feeding, diarrhea, irritability, tremor, rigidity, and seizures, and manage accordingly [see Warnings and Precautions (5.4)].

Teratogenic Effects - Pregnancy Category C: There are no adequate and well controlled studies in pregnant women. Methadone hydrochloride should be used during pregnancy only if the potential benefit justifies the potential risk to the fetus.

Methadone has been shown to be teratogenic in the hamster at doses 2 times the human daily oral dose (120 mg/day on a mg/m2 basis) and in mice at doses equivalent to the human daily oral dose (120 mg/day on a mg/m2 basis). Increased neonatal mortality and significant differences in behavioral tests have been reported in the offspring of male rodents that were treated with methadone prior to mating when compared to control animals. Methadone has been detected in human amniotic fluid and cord plasma at concentrations proportional to maternal plasma and in newborn urine at lower concentrations than corresponding maternal urine.

Dosage Adjustment during Pregnancy: The disposition of oral methadone has been studied in approximately 30 pregnant patients in 2nd and 3rd trimesters. Total body clearance of methadone was increased in pregnant patients compared to the same patients postpartum or to non-pregnant opioid-dependent women. The terminal half-life of methadone is decreased during 2nd and 3rd trimesters. The decrease in plasma half-life and increased clearance of methadone resulting in lower methadone trough levels during pregnancy can lead to withdrawal symptoms in some pregnant patients. The dosage may need to be increased or the dosing interval decreased in pregnant patients receiving methadone to achieve therapeutic effect [see Dosage and Administration (2.10)].

Effects on the Neonate: Babies born to mothers who have been taking opioids regularly prior to delivery may be physically dependent. Onset of withdrawal symptoms in infants is usually in the first days after birth. Monitor newborn for withdrawal signs and symptoms including: poor feeding, irritability, excessive crying, tremors, rigidity, hyper-active reflexes, increased respiratory rate, diarrhea, sneezing, yawning, vomiting, fever, and seizures. The intensity of the neonatal withdrawal syndrome does not always correlate with the maternal dose or the duration of maternal exposure. The duration of the withdrawal signs may vary from a few days to weeks or even months. There is no consensus on the appropriate management of infant withdrawal [see Warnings and Precautions (5.4)].

Human Data: Reported studies have generally compared the benefit of methadone to the risk of untreated addiction to illicit drugs; the relevance of these findings to pain patients prescribed methadone during pregnancy is unclear. Pregnant women involved in methadone maintenance programs have been reported to have significantly improved prenatal care leading to significantly reduced incidence of obstetric and fetal complications and neonatal morbidity and mortality when compared to women using illicit drugs. Several factors, including maternal use of illicit drugs, nutrition, infection and psychosocial circumstances, complicate the interpretation of investigations of the children of women who take methadone during pregnancy. Information is limited regarding dose and duration of methadone use during pregnancy, and most maternal exposure appears to occur after the first trimester of pregnancy.

A review of published data on experiences with methadone use during pregnancy by the Teratogen Information System (TERIS) concluded that maternal use of methadone during pregnancy as part of a supervised, therapeutic regimen is unlikely to pose a substantial teratogenic risk (quantity and quality of data assessed as “limited to fair”). However, the data are insufficient to state that there is no risk (TERIS, last reviewed October, 2002). A retrospective case series of 101 pregnant, opioid-dependent women who underwent inpatient opioid detoxification with methadone did not demonstrate any increased risk of miscarriage in the 2nd trimester or premature delivery in the 3rd trimester. Recent studies suggest an increased risk of premature delivery in opioid-dependent women exposed to methadone during pregnancy, although the presence of confounding factors makes it difficult to determine a causal relationship. Several studies have suggested that infants born to narcotic-addicted women treated with methadone during all or part of pregnancy have been found to have decreased fetal growth with reduced birth weight, length, and/or head circumference compared to controls. This growth deficit does not appear to persist into later childhood. Children prenatally exposed to methadone have been reported to demonstrate mild but persistent deficits in performance on psychometric and behavioral tests. In addition, several studies suggest that children born to opioid-dependent women exposed to methadone during pregnancy may have an increased risk of visual development anomalies; however, a causal relationship has not been assigned.

There are conflicting reports on whether Sudden Infant Death Syndrome occurs with an increased incidence in infants born to women treated with methadone during pregnancy. Abnormal fetal non-stress tests have been reported to occur more frequently when the test is performed 1 to 2 hours after a maintenance dose of methadone in late pregnancy compared to controls.

Animal Data: Methadone did not produce teratogenic effects in rat or rabbit models. Methadone produced teratogenic effects following large doses, in the guinea pig, hamster and mouse. One published study in pregnant hamsters indicated that a single subcutaneous dose of methadone ranging from 31 to 185 mg/kg (the 31 mg/kg dose is approximately 2 times a human daily oral dose of 120 mg/day on a mg/m2 basis) on day 8 of gestation resulted in a decrease in the number of fetuses per litter and an increase in the percentage of fetuses exhibiting congenital malformations described as exencephaly, cranioschisis, and “various other lesions.” The majority of the doses tested also resulted in maternal death. In another study, a single subcutaneous dose of 22 to 24 mg/kg methadone (estimated exposure was approximately equivalent to a human daily oral dose of 120 mg/day on a mg/m2 basis) administered on day 9 of gestation in mice also produced exencephaly in 11% of the embryos. However, no effects were reported in rats and rabbits at oral doses up to 40 mg/kg (estimated exposure was approximately 3 and 6 times, respectively, a human daily oral dose of 120 mg/day on a mg/m2 basis) administered during days 6 to 15 and 6 to 18, respectively.

Published animal data have reported increased neonatal mortality in the offspring of male rodents that were treated with methadone prior to mating. In these studies, the female rodents were not treated with methadone, indicating paternally- mediated developmental toxicity. Specifically, methadone administered to the male rat prior to mating with methadone- naïve females resulted in decreased weight gain in progeny after weaning. The male progeny demonstrated reduced thymus weights, whereas the female progeny demonstrated increased adrenal weights. Behavioral testing of these male and female progeny revealed significant differences in behavioral tests compared to control animals, suggesting that paternal methadone exposure can produce physiological and behavioral changes in progeny in this model. Other animal studies have reported that perinatal exposure to opioids including methadone alters neuronal development and behavior in the offspring. Perinatal methadone exposure in rats has been linked to alterations in learning ability, motor activity, thermal regulation, nociceptive responses and sensitivity to drugs.

Additional animal data demonstrates evidence for neurochemical changes in the brains of methadone-treated offspring, including changes to the cholinergic, dopaminergic, noradrenergic and serotonergic systems. Studies demonstrated that methadone treatment of male rats for 21 to 32 days prior to mating with methadone-naïve females did not produce any adverse effects, suggesting that prolonged methadone treatment of the male rat resulted in tolerance to the developmental toxicities noted in the progeny. Mechanistic studies in this rat model suggest that the developmental effects of “paternal” methadone on the progeny appear to be due to decreased testosterone production. These animal data mirror the reported clinical findings of decreased testosterone levels in human males on methadone maintenance therapy for opioid addiction and in males receiving chronic intraspinal opioids.

Additional data have been published indicating that methadone treatment of male rats (once a day for three consecutive days) increased embryolethality and neonatal mortality. Examination of uterine contents of methadone-naïve female mice bred to methadone-treated mice indicated that methadone treatment produced an increase in the rate of preimplantation deaths in all post-meiotic states.

8.2 Labor and Delivery

Opioids cross the placenta and may produce respiratory depression in neonates. Methadone hydrochloride is not for use in women during and immediately prior to labor, when shorter acting analgesics or other analgesic techniques are more appropriate. Opioid analgesics can prolong labor through actions that temporarily reduce the strength, duration, and frequency of uterine contractions. However this effect is not consistent and may be offset by an increased rate of cervical dilatation, which tends to shorten labor.

8.3 Nursing Mothers

Methadone is secreted into human milk. At maternal oral doses of 10 to 80 mg/day, methadone concentrations from 50 to 570 mcg/L in milk have been reported, which, in the majority of samples, were lower than maternal serum drug concentrations at steady state. Peak methadone levels in milk occur approximately 4 to 5 hours after an oral dose. Based on an average milk consumption of 150 mL/kg/day, an infant would consume approximately 17.4 mcg/kg/day which is approximately 2 to 3% of the oral maternal dose. Methadone has been detected in very low plasma concentrations in some infants whose mothers were taking methadone. Cases of sedation and respiratory depression in infants exposed to methadone through breast milk have been reported. Caution should be exercised when methadone is administered to a nursing woman.

Advise women who are being treated with methadone and who are breastfeeding or express a desire to breastfeed of the presence of methadone in human milk. Instruct breastfeeding mothers how to identify respiratory depression and sedation in their babies and when it may be necessary to contact their healthcare provider or seek immediate medical care. Breastfed infants of mothers using methadone should be weaned gradually to prevent development of withdrawal symptoms in the infant.

8.4 Pediatric Use

The safety, effectiveness, and pharmacokinetics of methadone in pediatric patients below the age of 18 years have not been established.

8.5 Geriatric Use

Clinical studies of methadone did not include sufficient numbers of subjects aged 65 and over to determine whether they respond differently compared to younger subjects. Other reported clinical experience has not identified differences in responses between elderly and younger patients. In general, start elderly patients at the low end of the dosing range, taking into account the greater frequency of decreased hepatic, renal, or cardiac function and of concomitant disease or other drug therapy in geriatric patients. Closely monitor elderly patients for signs of respiratory and central nervous system depression.

8.6 Renal Impairment

Methadone pharmacokinetics have not been extensively evaluated in patients with renal insufficiency. Since unmetabolized methadone and its metabolites are excreted in urine to a variable degree, start these patients on lower doses and with longer dosing intervals and titrate slowly while carefully monitoring for signs of respiratory and central nervous system depression.

8.7 Hepatic Impairment

Methadone has not been extensively evaluated in patients with hepatic insufficiency. Methadone is metabolized by hepatic pathways; therefore, patients with liver impairment may be at risk of increased systemic exposure to methadone after multiple dosing. Start these patients on lower doses and titrate slowly while carefully monitoring for signs of respiratory and central nervous system depression.

DRUG ABUSE AND DEPENDENCE

9.1 Controlled Substance

Methadone is a mu-agonist opioid with an abuse liability similar to other opioid agonists and is a Schedule II controlled substance. Methadone can be abused and is subject to misuse, addiction, and criminal diversion [see Warnings and Precautions (5.1)].

9.2 Abuse

All patients treated with opioids for pain management require careful monitoring for signs of abuse and addiction, since use of opioid analgesic products carries the risk of addiction even under appropriate medical use.

Drug abuse is the intentional non-therapeutic use of an over-the-counter or prescription drug, even once, for its rewarding psychological or physiological effects. Drug abuse includes, but is not limited to the following examples: the use of a prescription or over-the counter drug to get “high”, or the use of steroids for performance enhancement and muscle build up.

Drug addiction is a cluster of behavioral, cognitive, and physiological phenomena that develop after repeated substance use and include: a strong desire to take the drug, difficulties in controlling its use, persisting in its use despite harmful consequences, a higher priority given to drug use than to other activities and obligations, increased tolerance, and sometimes a physical withdrawal.

“Drug-seeking” behavior is very common in addicts and drug abusers. Drug-seeking tactics include emergency calls or visits near the end of office hours, refusal to undergo appropriate examination, testing or referral, repeated claims of lost prescriptions, tampering with prescriptions and reluctance to provide prior medical records or contact information for other treating physician(s). “Doctor shopping” (visiting multiple prescribers) to obtain additional prescriptions is common among drug abusers and people suffering from untreated addiction. Preoccupation with achieving adequate pain relief can be appropriate behavior in a patient with poor pain control.

Abuse and addiction are separate and distinct from physical dependence and tolerance. Physicians should be aware that addiction may not be accompanied by concurrent tolerance and symptoms of physical dependence in all addicts. In addition, abuse of opioids can occur in the absence of true addiction.

Methadone hydrochloride, like other opioids, can be diverted for non-medical use into illicit channels of distribution. Careful record-keeping of prescribing information, including quantity, frequency, and renewal requests, as required by state law, is strongly advised.

Risks Specific to Abuse of Methadone Hydrochloride: Abuse of methadone hydrochloride poses a risk of overdose and death. This risk is increased with concurrent abuse of methadone and alcohol or other substances. Methadone hydrochloride is for oral use only and must not be injected. Parenteral drug abuse is commonly associated with transmission of infectious diseases such as hepatitis and HIV.

Proper assessment and selection of the patient, proper prescribing practices, periodic re-evaluation of therapy, and proper dispensing and storage are appropriate measures that help to limit abuse of opioid drugs.

9.3 Dependence

Both tolerance and physical dependence can develop during chronic opioid therapy. Tolerance is the need for increasing doses of opioids to maintain a defined effect such as analgesia (in the absence of disease progression or other external factors). Tolerance may occur to both the desired and undesired effects of drugs, and may develop at different rates for different effects.

Physical dependence results in withdrawal symptoms after abrupt discontinuation or a significant dose reduction of a drug. Withdrawal also may be precipitated through the administration of drugs with opioid antagonist activity, e.g., naloxone, mixed agonist/antagonist analgesics (pentazocine, butorphanol, nalbuphine), or partial agonists (buprenorphine). Physical dependence may not occur to a clinically significant degree until after several days to weeks of continued opioid usage.

Methadone hydrochloride should not be abruptly discontinued [see Dosage and Administration (2.4)]. If methadone hydrochloride is abruptly discontinued in a physically dependent patient, an abstinence syndrome may occur. Some or all of the following can characterize this syndrome: restlessness, lacrimation, rhinorrhea, yawning, perspiration, chills, myalgia, and mydriasis. Other signs and symptoms also may develop, including irritability, anxiety, backache, joint pain, weakness, abdominal cramps, insomnia, nausea, anorexia, vomiting, diarrhea, or increased blood pressure, respiratory rate, or heart rate.

Infants born to mothers physically dependent on opioids will also be physically dependent and may exhibit respiratory difficulties and withdrawal symptoms [see Use in Specific Populations (8.1) and Warnings and Precautions (5.4)].

OVERDOSAGE

Clinical Presentation

Acute overdosage of methadone is manifested by respiratory depression, somnolence progressing to stupor or coma, maximally constricted pupils, skeletal-muscle flaccidity, cold and clammy skin, and sometimes, bradycardia and hypotension. In severe overdosage, particularly by the intravenous route, apnea, circulatory collapse, cardiac arrest, and death may occur.

Treatment of Overdose

In case of overdose, priorities are the re-establishment of a patent and protected airway and institution of assisted or controlled ventilation if needed. Employ other supportive measures (including oxygen, vasopressors) in the management of circulatory shock and pulmonary edema as indicated. Cardiac arrest or arrhythmias will require advanced life support techniques.

The opioid antagonists, such as naloxone, are specific antidotes to respiratory depression resulting from opioid overdose. Opioid antagonists should not be administered in the absence of clinically significant respiratory or circulatory depression secondary to methadone overdose. Such agents should be administered cautiously to patients who are known, or suspected to be, physically dependent on methadone hydrochloride. In such cases, an abrupt or complete reversal of opioid effects may precipitate an acute withdrawal syndrome.

Because the duration of reversal would be expected to be less than the duration of action of methadone in methadone hydrochloride, carefully monitor the patient until spontaneous respiration is reliably re-established. If the response to opioid antagonists is suboptimal or not sustained, additional antagonist should be given as directed in the product’s prescribing information.

In an individual physically dependent on opioids, administration of an opioid receptor antagonist may precipitate an acute withdrawal. The severity of the withdrawal produced will depend on the degree of physical dependence and the dose of the antagonist administered. If a decision is made to treat serious respiratory depression in the physically dependent patient, administration of the antagonist should be begun with care and by titration with smaller than usual doses of the antagonist.

DESCRIPTION

Methadone hydrochloride is chemically described as 6-(dimethylamino)-4,4-diphenyl-3-hepatanone hydrochloride. Methadone hydrochloride USP is a white, crystalline material that is water-soluble. Its molecular formula is C21H27NO• HCl and it has a molecular weight of 345.91. Methadone hydrochloride has a melting point of 235°C, and a pKa of 8.25 in water at 20°C. Its octanol/water partition coefficient at pH 7.4 is 117. A solution (1:100) in water has a pH between 4.5 and 6.5.

It has the following structural formula:

Each Methadone Hydrochloride Tablet USP contains 5 or 10 mg of methadone hydrochloride USP and the following inactive ingredients: magnesium stearate, microcrystalline cellulose and pregelatinized starch.

CLINICAL PHARMACOLOGY

12.1 Mechanism of Action

Methadone hydrochloride is a mu-agonist; a synthetic opioid analgesic with multiple actions qualitatively similar to those of morphine, the most prominent of which involves the central nervous system and organs composed of smooth muscle. The principal therapeutic uses for methadone are for analgesia and for detoxification or maintenance in opioid addiction. The methadone withdrawal syndrome, although qualitatively similar to that of morphine, differs in that the onset is slower, the course is more prolonged, and the symptoms are less severe.

Some data also indicate that methadone acts as an antagonist at the N-methyl-D-aspartate (NMDA) receptor. The contribution of NMDA receptor antagonism to methadone’s efficacy is unknown. Other NMDA receptor antagonists have been shown to produce neurotoxic effects in animals.

12.3 Pharmacokinetics

Absorption: Following oral administration the bioavailability of methadone ranges between 36 to 100% and peak plasma concentrations are achieved between 1 to 7.5 hours. Dose proportionality of methadone pharmacokinetics is not known. However, after administration of daily oral doses ranging from 10 to 225 mg, the steady-state plasma concentrations ranged between 65 to 630 ng/mL and the peak concentrations ranged between 124 to 1255 ng/mL. Effect of food on the bioavailability of methadone has not been evaluated.

Distribution: Methadone is a lipophilic drug and the steady-state volume of distribution ranges between 1.0 to 8.0 L/kg. In plasma, methadone is predominantly bound to α1-acid glycoprotein (85% to 90%). Methadone is secreted in saliva, breast milk, amniotic fluid and umbilical cord plasma.

Metabolism: Methadone is primarily metabolized by N-demethylation to an inactive metabolite, 2-ethylidene-1,5-dimethyl-3,3-diphenylpyrrolidene (EDDP). Cytochrome P450 enzymes, primarily CYP3A4, CYP2B6, and CYP2C19 and to a lesser extent CYP2C9 and CYP2D6, are responsible for conversion of methadone to EDDP and other inactive metabolites, which are excreted mainly in the urine. Methadone appears to be a substrate for P-glycoprotein but its pharmacokinetics do not appear to be significantly altered in case of P-glycoprotein polymorphism or inhibition.

Excretion: The elimination of methadone is mediated by extensive biotransformation, followed by renal and fecal excretion. Published reports indicate that after multiple dose administration the apparent plasma clearance of methadone ranged between 1.4 and 126 L/h, and the terminal half-life (T1/2) was highly variable and ranged between 8 to 59 hours in different studies. Methadone is a basic (pKa=9.2) compound and the pH of the urinary tract can alter its disposition in plasma. Also, since methadone is lipophilic, it has been known to persist in the liver and other tissues. The slow release from the liver and other tissues may prolong the duration of methadone action despite low plasma concentrations.

Drug Interactions: Cytochrome P450 Interactions: Methadone undergoes hepatic N-demethylation by cytochrome P450 (CYP) isoforms, principally CYP3A4, CYP2B6, CYP2C19, and to a lesser extent by CYP2C9 and CYP2D6. Coadministration of methadone with CYP inducers may result in more rapid metabolism and potential for decreased effects of methadone, whereas administration with CYP inhibitors may reduce metabolism and potentiate methadone’s effects. Although antiretroviral drugs such as efavirenz, nelfinavir, nevirapine, ritonavir, lopinavir+ritonavir combination are known to inhibit some CYPs, they are shown to reduce the plasma levels of methadone, possibly due to CYP induction activity [see Drug Interactions (7.2)]. Therefore, drugs administered concomitantly with methadone should be evaluated for interaction potential; clinicians are advised to evaluate individual response to drug therapy.

Cytochrome P450 Inducers: The following drug interactions were reported following coadministration of methadone with known inducers of cytochrome P450 enzymes:

Rifampin: In patients well-stabilized on methadone, concomitant administration of rifampin resulted in a marked reduction in serum methadone levels and a concurrent appearance of withdrawal symptoms.

Phenytoin: In a pharmacokinetic study with patients on methadone maintenance therapy, phenytoin administration (250 mg twice daily initially for 1 day followed by 300 mg daily for 3 to 4 days) resulted in an approximately 50% reduction in methadone exposure and withdrawal symptoms occurred concurrently. Upon discontinuation of phenytoin, the incidence of withdrawal symptoms decreased and methadone exposure increased to a level comparable to that prior to phenytoin administration.

St. John’s Wort, Phenobarbital, Carbamazepine: Administration of methadone with other CYP3A4 inducers may result in withdrawal symptoms.

Cytochrome P450 Inhibitors: Since the metabolism of methadone is mediated primarily by CYP3A4 isozyme, coadministration of drugs that inhibit CYP3A4 activity may cause decreased clearance of methadone.

Voriconazole: Repeat dose administration of oral voriconazole (400 mg every 12 hours for 1 day, then 200 mg every 12 hours for 4 days) increased the peak plasma concentration (Cmax) and AUC of (R)-methadone by 31% and 47%, respectively, in subjects receiving a methadone maintenance dose (30 to 100 mg daily). The Cmax and AUC of (S)-methadone increased by 65% and 103%, respectively. Increased plasma concentrations of methadone have been associated with toxicity including QT prolongation. Frequent monitoring for adverse events and toxicity related to methadone is recommended during coadministration. Dose reduction of methadone may be needed [see Drug Interactions (7.2)].

Antiretroviral drugs: Although antiretroviral drugs such as efavirenz, nelfinavir, nevirapine, ritonavir, telaprevir, lopinavir+ritonavir combination are known to inhibit some CYPs, they are shown to reduce the plasma levels of methadone, possibly due to CYP induction activity.

Abacavir, amprenavir, darunavir+ritonavir, efavirenz, nelfinavir, nevirapine, ritonavir, telaprevir, lopinavir+ritonavir, saquinavir+ritonavir, tipranvir+ritonavir combination: Coadministration of these anti-retroviral agents resulted in increased clearance or decreased plasma levels of methadone [see Drug Interactions (7.2)].

Didanosine and Stavudine: Methadone decreased the AUC and peak levels for didanosine and stavudine, with a more significant decrease for didanosine. Methadone disposition was not substantially altered [see Drug Interactions (7.2)].

Zidovudine: Methadone increased the AUC of zidovudine which could result in toxic effects [see Drug Interactions (7.2)].

NONCLINICAL TOXICOLOGY

13.1 Carcinogenesis, Mutagenesis, Impairment of Fertility

Carcinogenesis: The results of carcinogenicity assessment in B6C2F1 mice and Fischer 344 rats following dietary administration of two doses of methadone HCl have been published. Mice consumed 15 mg/kg/day or 60 mg/kg/day methadone for two years. These doses were approximately 0.6 and 2.5 times a human daily oral dose of 120 mg/day on a body surface area basis (mg/m2). There was a significant increase in pituitary adenomas in female mice treated with 15 mg/kg/day but not with 60 mg/kg/day. Under the conditions of the assay, there was no clear evidence for a treatment- related increase in the incidence of neoplasms in male rats. Due to decreased food consumption in males at the high dose, male rats consumed 16 mg/kg/day and 28 mg/kg/day of methadone for two years. These doses were approximately 1.3 and 2.3 times a human daily oral dose of 120 mg/day, based on body surface area comparison. In contrast, female rats consumed 46 mg/kg/day or 88 mg/kg/day for two years. These doses were approximately 3.7 and 7.1 times a human daily oral dose of 120 mg/day, based on body surface area comparison. Under the conditions of the assay, there was no clear evidence for a treatment-related increase in the incidence of neoplasms in either male or female rats.

Mutagenesis: There are several published reports on the potential genetic toxicity of methadone. Methadone tested positive in the in vivo mouse dominant lethal assay and the in vivo mammalian spermatogonial chromosome aberration test. Additionally, methadone tested positive in the E. coli DNA repair system and Neurospora crassa and mouse lymphoma forward mutation assays. In contrast, methadone tested negative in tests for chromosome breakage and disjunction and sex-linked recessive lethal gene mutations in germ cells of Drosophila using feeding and injection procedures.

Fertility: Published animal studies show that methadone treatment of males can alter reproductive function. Methadone produces a significant regression of sex accessory organs and testes of male mice and rats.

HOW SUPPLIED

16.1 Storage and Handling

Methadone hydrochloride tablets contain methadone which is a controlled substance. Like fentanyl, morphine, oxycodone, hydromorphone, and oxymorphone, methadone is controlled under Schedule II of the Federal Controlled Substances Act. Methadone hydrochloride may be targeted for theft and diversion by criminals [see Warnings and Precautions (5.1)].

Dispense in a tight, light-resistant container as defined in the USP/NF.

Store at 20° to 25°C (68° to 77°F). [See USP Controlled Room Temperature.]

16.2 How Supplied

Methadone Hydrochloride Tablets USP

5 mg tablets supplied as round, white, biconvex tablets debossed with product identification “54” above “210” on one side and scored on the other side.

: Bottle of 100 Tablets

: 4x25 Unit-Dose Tablets (reverse numbered)

10 mg tablets supplied as round, white, biconvex tablets debossed with product identification “54” above “142” on one side and scored on the other side.

: Bottle of 100 Tablets

: 4x25 Unit-Dose Tablets (reverse numbered)

DEA order form required.

PATIENT COUNSELING INFORMATION

Advise the patient to read the FDA-approved patient labeling (Medication Guide)

Addiction, Abuse, and Misuse: Inform patients that the use of methadone hydrochloride, even when taken as recommended, can result in addiction, abuse, and misuse, which can lead to overdose or death [see Warnings and Precautions (5.1)]. Instruct patients not to share methadone hydrochloride with others and to take steps to protect methadone hydrochloride from theft or misuse.

Life-threatening Respiratory Depression: Inform patients of the risk of life-threatening respiratory depression, including information that the risk is greatest when starting methadone hydrochloride or when the dose is increased, and that it can occur even at recommended doses [see Warnings and Precautions (5.2)]. Advise patients how to recognize respiratory depression and to seek medical attention if breathing difficulties develop.

Accidental Ingestion: Inform patients that accidental ingestion, especially in children, may result in respiratory depression or death [see Warnings and Precautions (5.2)]. Instruct patients to take steps to store methadone hydrochloride securely and to dispose of unused methadone hydrochloride by flushing the tablets down the toilet.

Symptoms of Arrhythmia: Instruct patients to seek medical attention immediately if they experience symptoms suggestive of an arrhythmia (such as palpitations, near syncope, or syncope) when taking methadone.

Neonatal Opioid Withdrawal Syndrome: Inform female patients of reproductive potential that prolonged use of methadone hydrochloride during pregnancy can result in neonatal opioid withdrawal syndrome, which may be life-threatening if not recognized and treated [see Warnings and Precautions (5.4)].

Interactions with Alcohol and other CNS Depressants: Inform patients that potentially serious additive effects may occur if methadone hydrochloride is used with alcohol or other CNS depressants, and not to use such drugs unless supervised by a health care provider.

Important Administration Instructions: Instruct patients how to properly take methadone hydrochloride, including the following:

•
Use methadone hydrochloride exactly as prescribed to reduce the risk of life-threatening adverse reactions (e.g., respiratory depression)
•
Do not discontinue methadone hydrochloride without first discussing the need for a tapering regimen with the prescriber
Hypotension: Inform patients that methadone hydrochloride may cause orthostatic hypotension and syncope. Instruct patients how to recognize symptoms of low blood pressure and how to reduce the risk of serious consequences should hypotension occur (e.g., sit or lie down, carefully rise from a sitting or lying position).

Driving or Operating Heavy Machinery: Inform patients that methadone hydrochloride may impair the ability to perform potentially hazardous activities such as driving a car or operating heavy machinery. Advise patients not to perform such tasks until they know how they will react to the medication.

Constipation: Advise patients of the potential for severe constipation, including management instructions and when to seek medical attention.

Anaphylaxis: Inform patients that anaphylaxis has been reported with ingredients contained in methadone hydrochloride. Advise patients how to recognize such a reaction and when to seek medical attention.

Breastfeeding: Instruct nursing mothers using methadone hydrochloride to watch for signs of methadone toxicity in their infants, which include increased sleepiness (more than usual), difficulty breastfeeding, breathing difficulties, or limpness. Instruct nursing mothers to talk to the baby’s healthcare provider immediately if they notice these signs. If they cannot reach the healthcare provider right away, instruct them to take the baby to the emergency room or call 911 (or local emergency services).

Disposal of Unused Methadone Hydrochloride: Advise patients to flush the unused tablets down the toilet when methadone hydrochloride is no longer needed.

Distr. by: West-Ward

Pharmaceuticals Corp.

Eatontown, NJ 07724

4077442//10

Revised April 2016

MEDICATION GUIDE

Methadone Hydrochloride Tablets USP CII

(METH a done)

Rx Only

Methadone hydrochloride is:

•
A strong prescription pain medicine that contains an opioid (narcotic) that is used to manage pain severe enough to require daily around-the-clock, long-term treatment with an opioid, when other pain treatments such as non-opioid pain medicines or immediate-release opioid medicines do not treat your pain well enough or you cannot tolerate them.
•
A long-acting opioid pain medicine that can put you at risk for overdose and death. Even if you take your dose correctly as prescribed you are at risk for opioid addiction, abuse, and misuse than can lead to death.
•
Not for use to treat pain that is not around-the-clock.
•
Also used to manage drug addiction.

Important information about methadone hydrochloride:

•
Get emergency help right away if you take too much methadone hydrochloride (overdose). When you first start taking methadone hydrochloride, when your dose is changed, or if you take too much (overdose), serious or life-threatening breathing problems that can lead to death may occur.
•
Never give anyone your methadone hydrochloride. They could die from taking it. Store methadone hydrochloride away from children and in a safe place to prevent stealing or abuse. Selling or giving away methadone hydrochloride is against the law.

Do not take methadone hydrochloride if you have:

•
severe asthma, trouble breathing, or other lung problems.
•
a bowel blockage or have narrowing of the stomach or intestines.

Before taking methadone hydrochloride, tell your healthcare provider if you have a history of:

•
head injury, seizures
•
liver, kidney, thyroid problems
•
problems urinating
•
pancreas or gallbladder problems
•
heart rhythm problems (Long QT syndrome)
•
abuse of street or prescription drugs, alcohol addiction, or mental health problems.

Tell your healthcare provider if you are:

•
pregnant or planning to become pregnant. Prolonged use of methadone hydrochloride during pregnancy can cause withdrawal symptoms in your newborn baby that could be life-threatening if not recognized and treated.
•
breastfeeding. Methadone hydrochloride passes into breast milk and may harm your baby.
•
taking prescription or over-the-counter medicines, vitamins, or herbal supplements. Taking methadone hydrochloride with certain other medicines may cause serious side effects.

When taking methadone hydrochloride:

•
Do not change your dose. Take methadone hydrochloride exactly as prescribed by your healthcare provider.
•
Do not take more than your prescribed dose in 24 hours. If you take methadone hydrochloride for pain and miss a dose, take methadone hydrochloride as soon as possible and then take your next dose 8 or 12 hours later as directed by your healthcare provider. If it is almost time for your next dose, skip the missed dose and go back to your regular dosing schedule.
•
If you take methadone hydrochloride for opioid addiction and miss a dose, take your next dose the following day as scheduled. Do not take extra doses. Taking more than the prescribed dose may cause you to overdose because methadone hydrochloride builds up in your body over time.
•
Do not crush, dissolve, snort or inject methadone hydrochloride because this may cause you to overdose and die.
•
Call your healthcare provider if the dose you are taking does not control your pain.
•
Do not stop taking methadone hydrochloride without talking to your healthcare provider.
•
After you stop taking methadone hydrochloride, flush any unused tablets down the toilet.

While taking methadone hydrochloride Do Not:

•
Drive or operate heavy machinery, until you know how methadone hydrochloride affects you. Methadone hydrochloride can make you sleepy, dizzy, or lightheaded.
•
Drink alcohol or use prescription or over-the-counter medicines that contain alcohol. Using products containing alcohol during treatment with methadone hydrochloride may cause you to overdose and die.

The possible side effects of methadone hydrochloride are:

•
constipation, nausea, sleepiness, vomiting, tiredness, headache, dizziness, abdominal pain. Call your healthcare provider if you have any of these symptoms and they are severe.

Get emergency medical help if you have:

•
trouble breathing, shortness of breath, fast heartbeat, chest pain, swelling of your face, tongue or throat, extreme drowsiness, light-headedness when changing positions, or you are feeling faint.

These are not all the possible side effects of methadone hydrochloride. Call your doctor for medical advice about side effects. You may report side effects to FDA at 1-800-FDA-1088. For more information go to dailymed.nlm.nih.gov.

Distributed by: West-Ward Pharmaceuticals Corp., Eatontown, NJ 07724, 1-800-962-8364

This Medication Guide has been approved by the U.S. Food and Drug Administration. Issue: April 2014

4077442//10